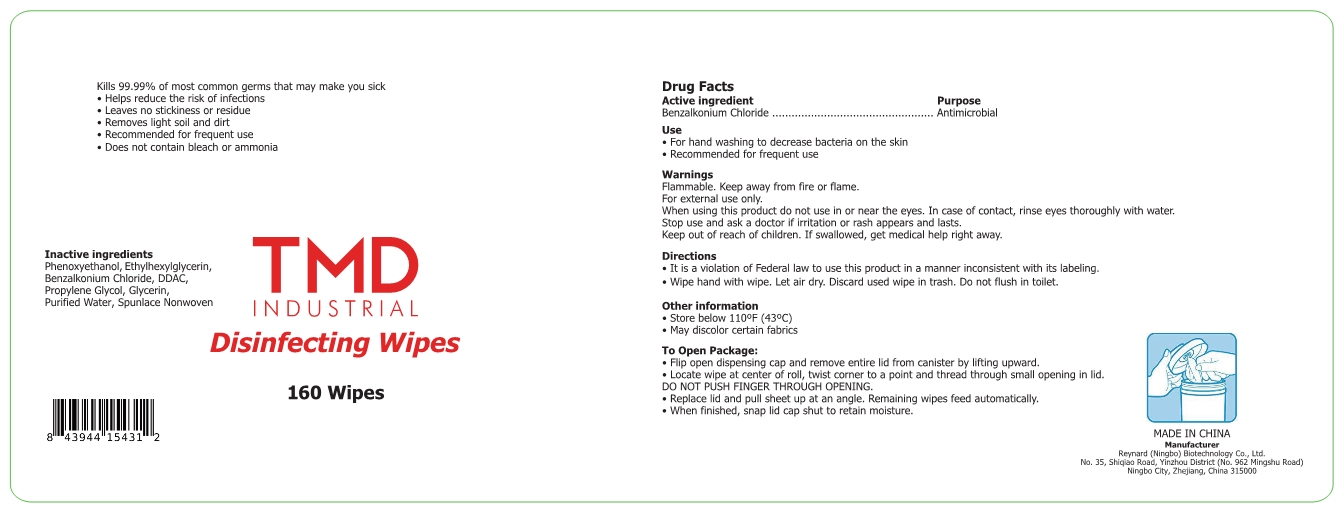 DRUG LABEL: Disinfecting Wipes
NDC: 55485-003 | Form: CLOTH
Manufacturer: Reynard (Ningbo) Biotechnology Co., Ltd.
Category: otc | Type: HUMAN OTC DRUG LABEL
Date: 20200529

ACTIVE INGREDIENTS: BENZALKONIUM CHLORIDE 0.12 g/160 1; ETHYLHEXYLGLYCERIN 0.12 g/160 1; GLYCERIN 0.12 g/160 1; PHENOXYETHANOL 0.6 g/160 1; PROPYLENE GLYCOL 0.12 g/160 1; DIDECYLDIMONIUM CHLORIDE 0.24 g/160 1
INACTIVE INGREDIENTS: WATER

DOSAGE AND ADMINISTRATION

Store below 110°F (43°0C)

INACTIVE INGREDIENT

Purified water

Spunlace non-woven

INDICATIONS AND USAGE

Wipe hand with wipe. Let air dry. Discard used wipe in trash. Do not flush in tilet.

ACTIVE INGREDIENT

phenoxyethanol

Ethylhexylglycerin

Benzalkonium chloride

DDAC

Propylene glycol

glycerin

PURPOSE

Disinfection
Sterilization
No Rinseing

WARNINGS

1.Flammable. Keep away from fire or flame.For external use only.
2.When using this product do not use in or near the eyes. In case of contact, rinse eyes thoroughly with water.Stop use and ask a doctor if iritation or rash appears and lasts.
3.Keep out of reach of children. If swallowed, get medical help right away.

keep out of reach of children